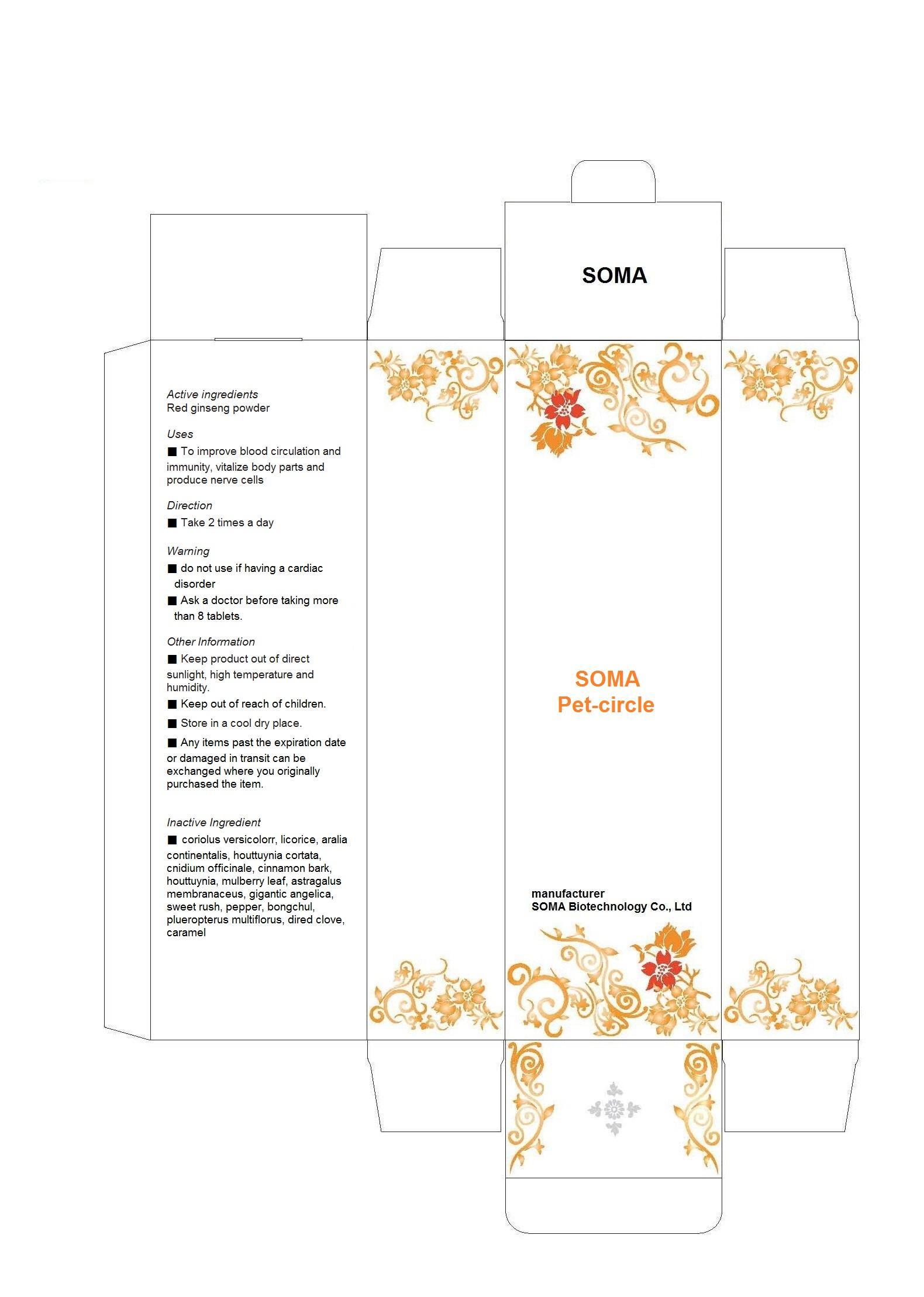 DRUG LABEL: SOMA Pet-circle
NDC: 58370-3001 | Form: POWDER
Manufacturer: SOMA Biotechnology Co., Ltd
Category: otc | Type: HUMAN OTC DRUG LABEL
Date: 20130502

ACTIVE INGREDIENTS: ASIAN GINSENG 5.67 g/100 g
INACTIVE INGREDIENTS: TRAMETES VERSICOLOR FRUITING BODY; GLYCYRRHIZA GLABRA; ARALIA CORDATA ROOT; HOUTTUYNIA CORDATA FLOWERING TOP; CNIDIUM OFFICINALE WHOLE; CINNAMON; MORUS AUSTRALIS LEAF; ASTRAGALUS PROPINQUUS ROOT; ANGELICA SINENSIS ROOT; ACORUS GRAMINEUS ROOT; PEPPERS; ZEDOARY; POLYGONUM CUSPIDATUM WHOLE; CLOVE; CARAMEL

Drug Facts

ACTIVE INGREDIENT

red ginseng powder

INACTIVE INGREDIENT

coriolus versicolorr, licorice, aralia continentalis, houttuynia cortata, cnidium officinale, cinnamon bark, houttuynia, mulberry leaf, astragalus membranaceus, gigantic angelica, sweet rush, pepper, bongchul, plueropterus multiflorus, dired clove, caramel

PURPOSE

To improve blood circulation and immunity, vitalize body parts and produce nerve cells

keep out of reach of the children

INDICATIONS AND USAGE

■ Take 2 times a day

■ do not use if having a cardiac disorder
■ Ask a doctor before taking more than 8 tablets.

DOSAGE AND ADMINISTRATION

for oral use only